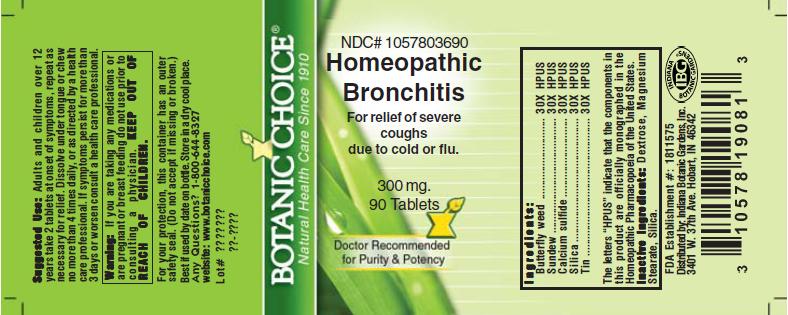 DRUG LABEL: Homeopathic Bronchitis Formula
NDC: 10578-036 | Form: TABLET
Manufacturer: Indiana Botanic Gardens
Category: homeopathic | Type: HUMAN OTC DRUG LABEL
Date: 20110325

ACTIVE INGREDIENTS: ASCLEPIAS TUBEROSA FLOWERING TOP 30 [hp_X]/1 1; DROSERA ROTUNDIFOLIA 30 [hp_X]/1 1; CALCIUM SULFIDE 30 [hp_X]/1 1; SILICON DIOXIDE 30 [hp_X]/1 1; TIN 30 [hp_X]/1 1
INACTIVE INGREDIENTS: DEXTROSE; MAGNESIUM STEARATE ; SILICON DIOXIDE 

Homeopathic Bronchitis Formula

ACTIVE INGREDIENT

I n g r e d i e n t s :

Butterfly weed..................... 30X HPUS
Sundew..................... 30X HPUS
Calcium sulfide.......... 30X HPUS
Silica....................................... 30X HPUS
Tin................... 30X HPUS

The letters “HPUS” indicate that the components in
this product are officially monographed in the
Homeopathic Pharmacopoeia of the United States.

PURPOSE

For relief of severe coughs due to cold or flu

KEEP OUT OF
REACH OF CHILDREN.

INDICATIONS AND USAGE

For relief of severe coughs due to cold or flu

WARNINGS

Warning: If you are taking any medications or
are pregnant or breast feeding do not use prior to
consulting a physician.

DOSAGE AND ADMINISTRATION

Suggested Use: Adults and children over 12
years, take 2 tablets at onset of symptoms, repeat as necessary
for relief. Dissolve under tongue or
chew no more than 4 times daily, or as directed by a health care
professional. Take 15 minutes before or after meals.
If symptoms persist for more than 3 days or worsen consult a
health professional.

Inactive Ingredients: Dextrose, Magnesium
Stearate, Silica.

PACKAGE LABEL

NDC# 1057803690

Homeopathic Bronchitis Formula

For relief of severe coughs due to cold or flu

300 mg.
90 Tablets

USER SAFETY WARNINGS

For your protection, this container has an outer
safety seal. (Do not accept if missing or broken.)
Best if used by date on bottle. Store in a dry cool place.
Any Questions? 1-800-644-8327
website: www.botanicchoice.com

FDA Establishment #: 1811575

Distributed by: Indiana Botanic Gardens, Inc.
3401 W. 37th Ave. Hobart, IN 46342